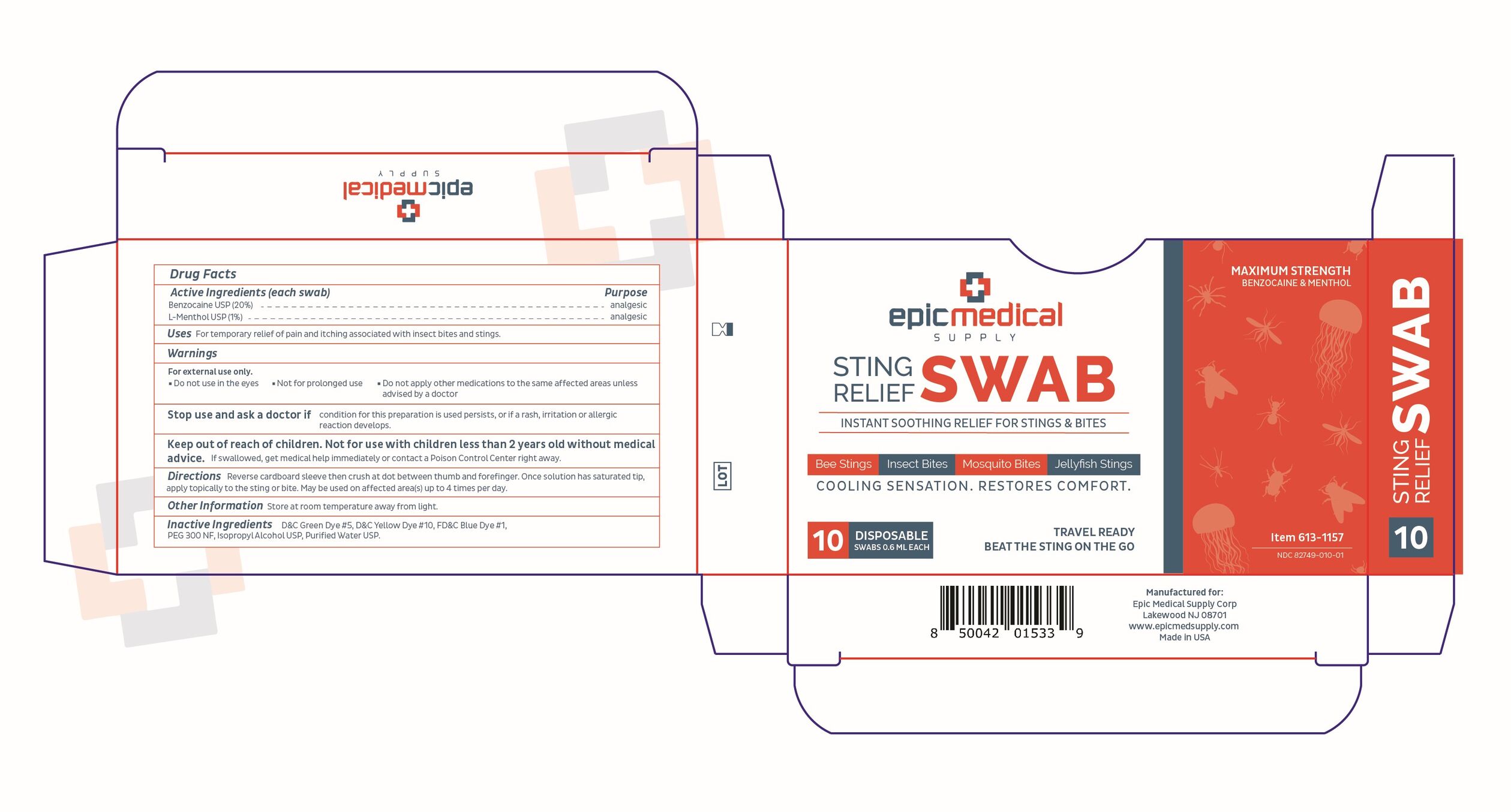 DRUG LABEL: Sting Relief Swab
NDC: 82749-010 | Form: SWAB
Manufacturer: Epic Medical Supply Corp
Category: otc | Type: HUMAN OTC DRUG LABEL
Date: 20250107

ACTIVE INGREDIENTS: MENTHOL, UNSPECIFIED FORM 0.006 g/0.6 mL; BENZOCAINE 0.12 g/0.6 mL
INACTIVE INGREDIENTS: POLYETHYLENE GLYCOL 300; WATER; FD&C BLUE NO. 1; ISOPROPYL ALCOHOL; D&C GREEN NO. 5; D&C YELLOW NO. 10

Sting Relief

Active Ingredients (each swab)

Benzocaine USP (20%), L-Menthol USP (1%)

Purpose

analgesic

Uses

For temporary relief of pain and itching associated with insect bites and stings.

Warnings

For external use only

- do not use in the eyes
- not for prolonged use
- do not apply other medications to the same affected areas unless advised by a doctor

Stop use and ask a doctor ifcondition for this preparation is used persists, or if a rash, irritation or allergic reaction develops.

Keep out of reach of children. Not for use with children less than 2 years old without medical advice.If swallowed, get medical help immediately or contact a Poison Control Center right away.

Directions

Reverse cardboard sleeve then crush at dot between thumb and forefinger. Once solution has saturated tip, apply topically to the sting or bite. May be used on affected area(s) up to 4 times per day.

Other Information

Store at room temperature away from light.

Inactive Ingredients

D&C Green Dye #5, D&C Yellow Dye #10, FD&C Blue Dye #1, PEG 300 NF, Isopropyl Alcohol USP, Purified Water USP.